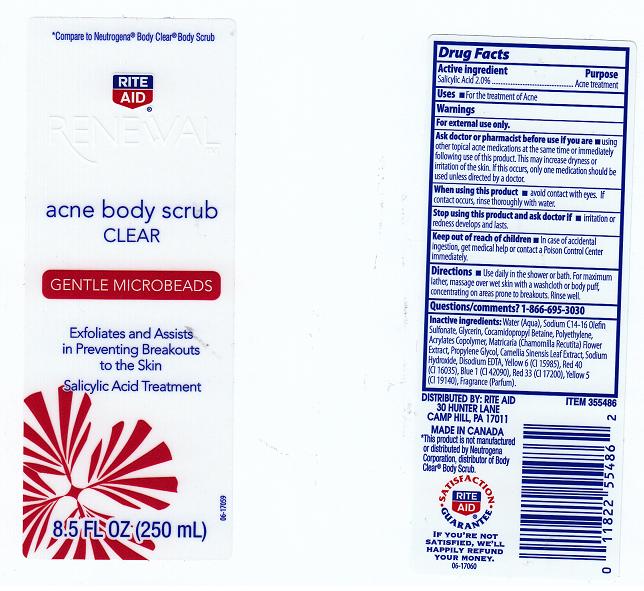 DRUG LABEL: RITE AID RENEWAL
NDC: 11822-8270 | Form: LIQUID
Manufacturer: RITE AID
Category: otc | Type: HUMAN OTC DRUG LABEL
Date: 20120613

ACTIVE INGREDIENTS: SALICYLIC ACID 2 mL/100 mL
INACTIVE INGREDIENTS: WATER; SODIUM C14-16 OLEFIN SULFONATE; GLYCERIN; COCAMIDOPROPYL BETAINE; HIGH DENSITY POLYETHYLENE; CARBOMER COPOLYMER TYPE A; CHAMOMILE; PROPYLENE GLYCOL; GREEN TEA LEAF; SODIUM HYDROXIDE; EDETATE DISODIUM; FD&C YELLOW NO. 6; FD&C RED NO. 40; FD&C BLUE NO. 1; D&C RED NO. 33; FD&C YELLOW NO. 5

DRUG LISTING

ACTIVE INGREDIENT

SALICYLIC ACID 2%

PURPOSE

ACNE TREATMENT

USES

FOR THE TREATMENT OF ACNE.

WARNINGS

FOR EXTERNAL USE ONLY.

ASK DOCTOR OR PHARMACIST BEFORE USE IF YOU ARE

USING OTHER TOPICAL ACNE MEDICATIONS AT THE SAME TIME OR IMMEDIATELY FOLLOWING USE OF THIS PRODUCT. THIS MAY INCREASE DRYNESS OR IRRITATION OF THE SKIN. IF THIS OCCURS, ONLY ONE MEDICATION SHOULD BE USED UNLESS DIRECTED BY A DOCTOR.

WHEN USING THIS PRODUCT

AVOID CONTACT WITH EYES. IF CONTACT OCCURS, RINSE THOROUGHLY WITH WATER.

STOP USING THIS PRODUCT AND ASK DOCTOR IF

IRRITATION OR REDNESS DEVELOPS AND LASTS.

KEEP OUT OF REACH OF CHILDREN

IN CASE OF ACCIDENTAL INGESTION, GET MEDICAL HELP OR CONTACT A POISON CONTROL CENTER IMMEDIATELY.

DIRECTIONS

USE DAILY IN THE SHOWER OR BATH. FOR MAXIMUM LATHER, MASSAGE OVER WET SKIN WITH A WASHCLOTH OR BODY PUFF, CONCENTRATING ON AREAS PRONE TO BREAKOUTS. RINSE WELL.

QUESTIONS/COMMENTS?

1-866-695-3030

INACTIVE INGREDIENTS:

WATER (AQUA), SODIUM C14-16 OLEFIN SULFONATE, GLYCERIN, COCAMIDOPROPYL BETAINE, POLYETHYLENE, ACRYLATES COPOLYMER, MATRICARIA (CHAMOMILLA RECUTITA) FLOWER EXTRACT, PROPYLENE GLYCOL, CAMELLIA SINENSIS LEAF EXTRACT, SODIUM HYDROXIDE, DISODIUM EDTA, YELLOW 6 (CI 15985), RED 40 (CI 16035), BLUE 1 (CI 42090), RED 33 (CI 17200), YELLOW 5 (CI 19140), FRAGRANCE (PARFUM).